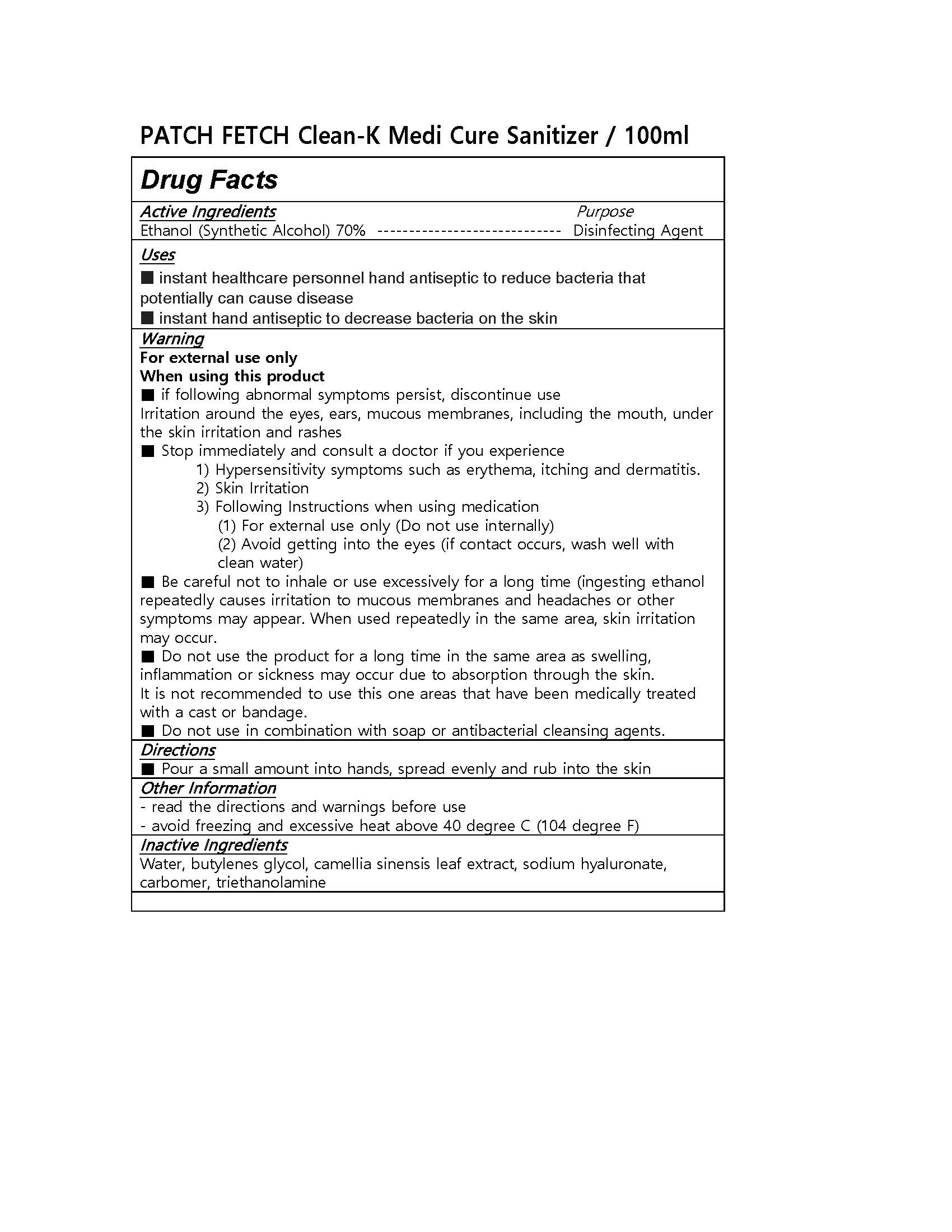 DRUG LABEL: PATCHFETCH Clean-K Medi Cure Sanitizer
NDC: 73140-0004 | Form: GEL
Manufacturer: The Times Co., Ltd.
Category: otc | Type: HUMAN OTC DRUG LABEL
Date: 20200331

ACTIVE INGREDIENTS: ALCOHOL 70 g/100 mL
INACTIVE INGREDIENTS: WATER; HYALURONATE SODIUM; TROLAMINE

Drug Facts

ACTIVE INGREDIENT

alcohol 62%

INACTIVE INGREDIENT

Water, butylenes glycol, camellia sinensis leaf extract, sodium hyaluronate, carbomer, triethanolamine

PURPOSE

Antiseptic

instant healthcare personnel hand antiseptic to reduce bacteria that potentially can cause disease

instant hand antiseptic to decrease bacteria on the skin
recommended for repeated use

KEEP OUT OF REACH OF THE CHILDREN

INDICATIONS AND USAGE

Apply to clean, dry hands. Apply sufficient amount to thoroughly wet all surfaces of hands and fingers. Rub onto hands until dry.

Supervise children in the use of this product.

WARNINGS

For external use only.

Flammable, keep away from fire or flame.

When using this product keep out of eyes. If contact with eyes occurs, rinse promptly and thoroughly with water.

Stop use and ask a doctor if significant irritation or sensitization develops.

Keep out of reach of children. If swallowed, get medical help or contact a Poison Control Center right away.

DOSAGE AND ADMINISTRATION

Pour a small amount into hands, spread evenly and rub into the skin